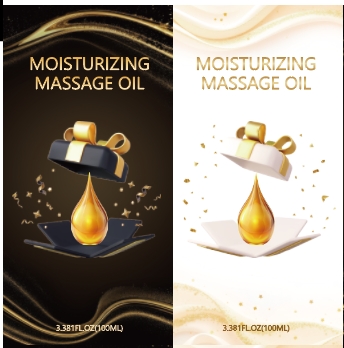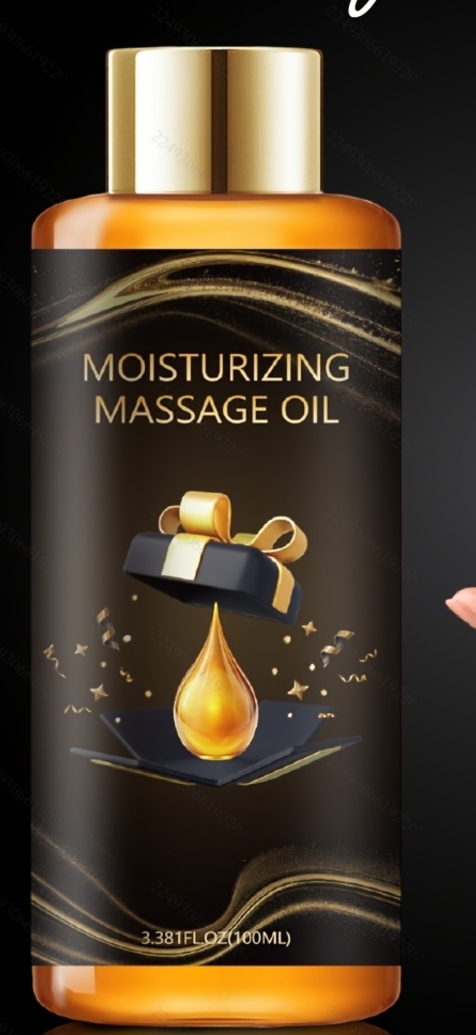 DRUG LABEL: Moisturizing Massage Oil
NDC: 84025-294 | Form: OIL
Manufacturer: Guangzhou Yanxi Biotechnology Co., Ltd
Category: otc | Type: HUMAN OTC DRUG LABEL
Date: 20241223

ACTIVE INGREDIENTS: CARBOMER 3 mg/100 mL; GLYCERIN 5 mg/100 mL
INACTIVE INGREDIENTS: WATER

DOSAGE AND ADMINISTRATION

use as a normal body oil

WARNINGS

keep out of children

INACTIVE INGREDIENT

Aqua

INDICATIONS AND USAGE

for daily bady care

keep out of children

PURPOSE

moisturizing and hydration for body